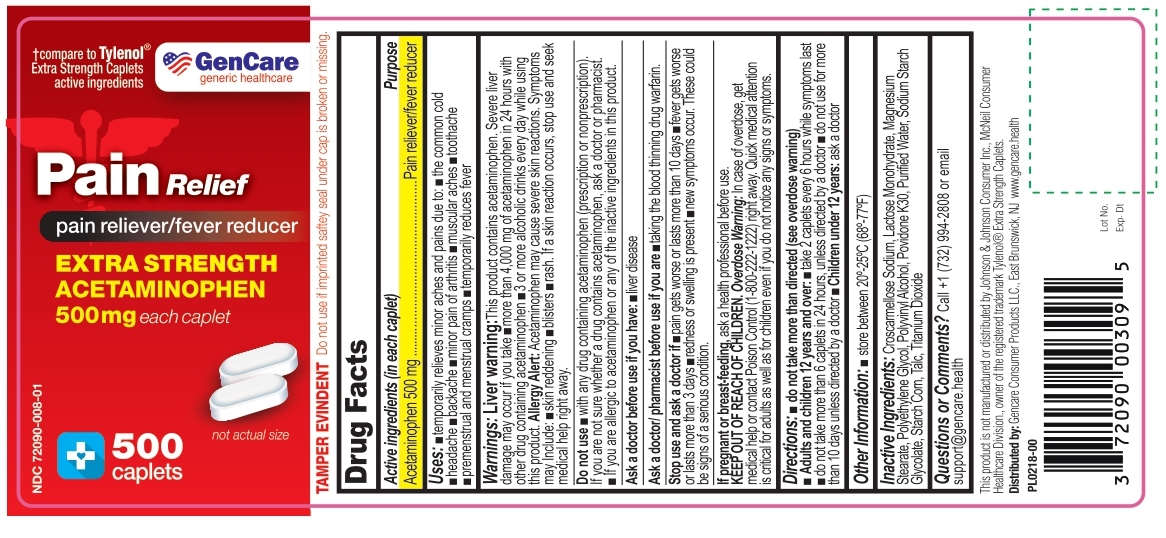 DRUG LABEL: ACETAMINOPHEN 500 MG
NDC: 72090-008 | Form: TABLET
Manufacturer: Pioneer Life Sciences, LLC
Category: otc | Type: HUMAN OTC DRUG LABEL
Date: 20251223

ACTIVE INGREDIENTS: ACETAMINOPHEN 500 mg/1 1
INACTIVE INGREDIENTS: CROSCARMELLOSE SODIUM; LACTOSE MONOHYDRATE; MAGNESIUM STEARATE; POLYETHYLENE GLYCOL, UNSPECIFIED; POLYVINYL ALCOHOL, UNSPECIFIED; POVIDONE K30; WATER; SODIUM STARCH GLYCOLATE TYPE A CORN; STARCH, CORN; TALC; TITANIUM DIOXIDE

Extra Strength ACETAMINOPHEN 500 MG Caplet

Drug Facts

Active ingredient (in each caplet)

Acetaminophen 500 mg

Purpose

Pain reliever/fever reducer

Uses

- temporarily relieves minor aches and pains due to:
- the common cold
- headache
- backache
- minor pain of arthritis
- muscular aches
- toothache
- premenstrual and menstrual cramps
- temporarily reduces fever

Warnings

Liver warning: This product contains acetaminophen. Severe liver damage may occur if you take

- more than 4,000 mg of acetaminophen in 24 hours with other drugs containing acetaminophen
- 3 or more alcoholic drinks every day while using this product

Allergy alert: Acetaminophen may cause severe skin reactions. Symptoms may include:

- skin reddening
- blisters
- rash

- If a skin reaction occurs, stop use and seek medical help right away.

Do not use

- with any other drug containing acetaminophen (prescription or nonprescription). If you are not sure whether a drug contains acetaminophen, ask a doctor or pharmacist.
- If you are allergic to acetaminophen or any of the inactive ingredient in this product.

Ask a doctor before use if you have

- liver disease

Ask a doctor/pharmacist before use if you are

- taking the blood thinning drug warfarin

Stop use and ask a doctor if

- pain gets worse or lasts more than 10 days
- fever gets worse or lasts more than 3 days
- redness or swelling is present
- new symptoms occur

These could be signs of a serious condition.

PREGNANCY OR BREAST FEEDING

If pregnant or breast-feeding, ask a health professional before use.

KEEP OUT OF REACH OF CHILDREN.

Overdose warning: In case of overdose, get medical help or contact a Poison Control (1-800-222-1222) right away. Quick medical attention is critical for adults as well as for children even if you do not notice any signs or symptoms.

Directions

- do not take more than directed (see overdose warning)

Adults and children 12 years and over:

- take 2 Caplets every 6 hours while symptoms last
- do not take more than 6 caplets in hours, unless directed by a doctor
- do not use for more than 10 days unless directed by a doctor

Children under 12 Years

- ask a doctor

Other information

- store at 20º - 25ºC (68º -77ºF)

Inactive ingredients

Croscarmellose Sodium, Lactose Monohydrate, Magnesium Stearate, Polyethylene Glycol, Polyvinyl Alcohol, Povidone k30, Purified water, Sodium Starch Glycolate, Starch Corn, Talc, Titanium Dioxide

Questions or comments?

Call +1 (732) 994-2808 or email support@gencare.health

TAMPER EVIDENT: Do not use if imprinted saftey seal under cap is broken or missing.

This product is not manufactured or distributed by Johnson & Johnson Consumer Inc., McNeil Consumer Healthcare Division., owner of the registered trademark Tyleno® Extra Strength Caplets.

Distributed by:

GenCare Consumer Products LLC

40E Cotters Ln Suite A,

East Brunswick, NJ 08816